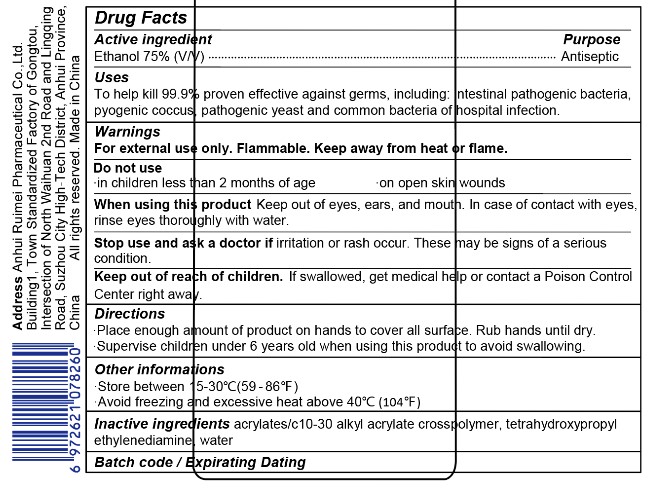 DRUG LABEL: Hand Sanitizer
NDC: 77467-002 | Form: GEL
Manufacturer: Anhui Ruimei Pharmaceutical Co.,Ltd
Category: otc | Type: HUMAN OTC DRUG LABEL
Date: 20200507

ACTIVE INGREDIENTS: ALCOHOL 75 mL/100 mL
INACTIVE INGREDIENTS: CARBOMER INTERPOLYMER TYPE A (ALLYL SUCROSE CROSSLINKED) 0.5 mL/100 mL; EDETOL 0.25 mL/100 mL; WATER

hand sanitizer

Active Ingredient(s)

Ethanol 75%(v/v) purpose:Antisepic

Purpose

Antiseptic, Hand Sanitizer

Use

To help kill 99.9% proven effective against germs, including: intestinal pathogenic bacteria, pyogenic coccus, pathogenic yeast and common bacteria of hospital infection.

Warnings

For external use only. Flammable. Keep away from heat or flame

Do not use

- in children less than 2 months of age
- on open skin wounds

When using this product keep out of eyes, ears, and mouth. In case of contact with eyes, rinse eyes thoroughly with water.
Stop use and ask a doctor if irritation or rash occurs. These may be signs of a serious condition.
Keep out of reach of children. If swallowed, get medical help or contact a Poison Control Center right away.

Stop use and ask a doctor if irritation or rash occurs. These may be signs of a serious condition.

Keep out of reach of children. If swallowed, get medical help or contact a Poison Control Center right away.

Directions

- Place enough product on hands to cover all surfaces. Rub hands together until dry.
- Supervise children under 6 years of age when using this product to avoid swallowing.

Other information

- Store between 15-30C (59-86F)
- Avoid freezing and excessive heat above 40C (104F)

Inactive ingredients

ACRYLATES/C10-30 ALKYL ACRYLATE CROSSPOLYMER,TETRAHYDROXYPROPYL ETHYLENEDIAMINE,WATER

Package Label - Principal Display Panel

500mL NDC: 77467-002-01